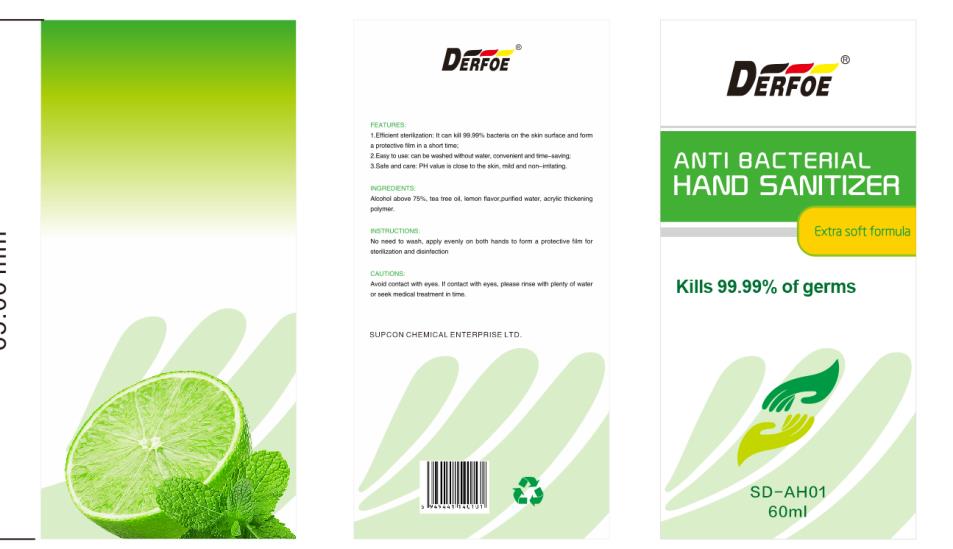 DRUG LABEL: Anti-Bacterial Hand Sanitizer
NDC: 55475-001 | Form: LIQUID
Manufacturer: Supcon Advanced Materials Technology Co., Ltd.
Category: otc | Type: HUMAN OTC DRUG LABEL
Date: 20200415

ACTIVE INGREDIENTS: ALCOHOL 45 mL/60 mL
INACTIVE INGREDIENTS: WATER

DOSAGE AND ADMINISTRATION

Keep it sealed and store it in a cool, dry,well-ventilated environment away from light.

INACTIVE INGREDIENT

Pure water and Additive

INDICATIONS AND USAGE

take this product in the palm of your hand,and coat each part evenly with your hands for 1 minute.

ACTIVE INGREDIENT

Alcohol

keep out of children

PURPOSE

Disinfection
Sterilization
No Rinseing

WARNINGS

1. This product for external use, should not be taken orally ; it should be keptout of reach of children.
2. Use with caution if you areallergic to alcohol.
3. This productcontains ethanol, please keep awayfrom fire.
4. Keep in a cool and dry place.